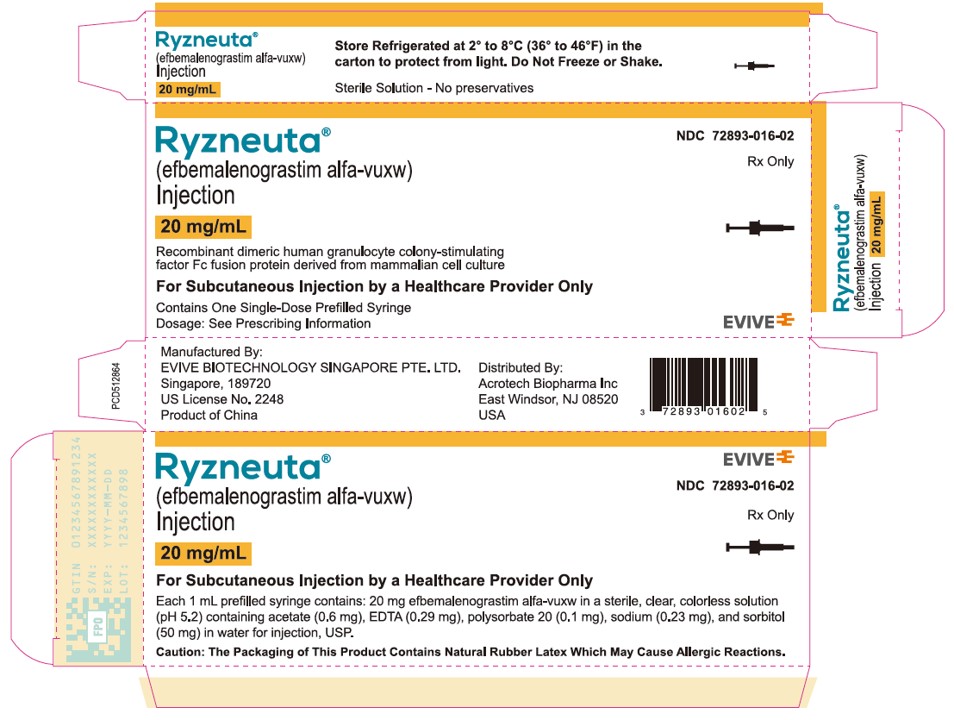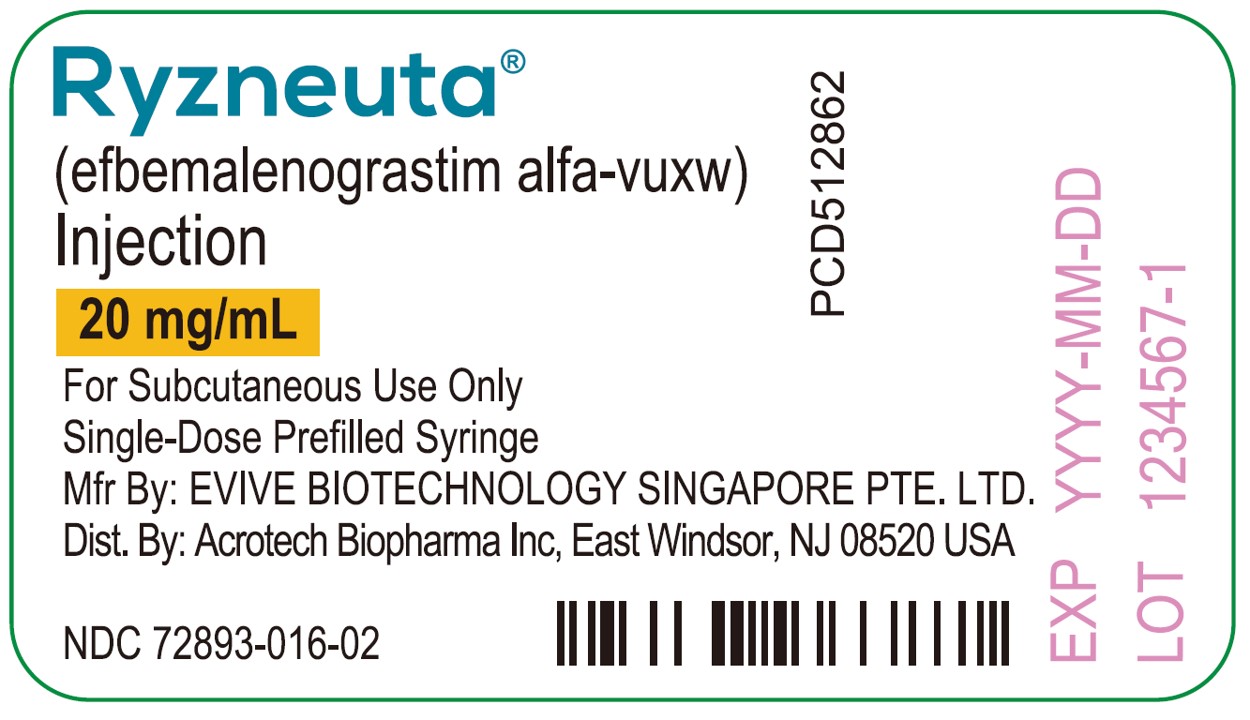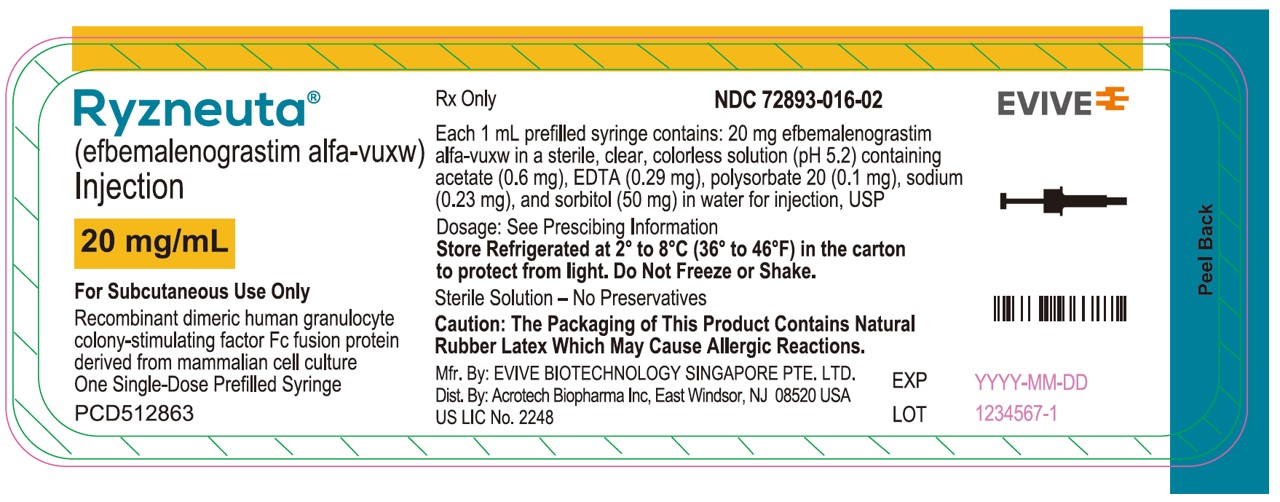 DRUG LABEL: RYZNEUTA
NDC: 72893-016 | Form: INJECTION
Manufacturer: Acrotech Biopharma Inc
Category: prescription | Type: HUMAN PRESCRIPTION DRUG LABEL
Date: 20251127

ACTIVE INGREDIENTS: EFBEMALENOGRASTIM ALFA 20 mg/1 mL
INACTIVE INGREDIENTS: ACETATE ION 0.6 mg/1 mL; EDETIC ACID 0.29 mg/1 mL; POLYSORBATE 20 0.1 mg/1 mL; SODIUM 0.23 mg/1 mL; SORBITOL 50 mg/1 mL; WATER

HIGHLIGHTS OF PRESCRIBING INFORMATION

These highlights do not include all the information needed to use RYZNEUTA ®safely and effectively. See full prescribing information for RYZNEUTA.
RYZNEUTA ®(efbemalenograstim alfa-vuxw) injection, for subcutaneous use
Initial U.S. Approval: 2023

1. INDICATIONS AND USAGE

RYZNEUTA is a leukocyte growth factor indicated to decrease the incidence of infection, as manifested by febrile neutropenia, in adult patients with non-myeloid malignancies receiving myelosuppressive anti-cancer drugs associated with a clinically significant incidence of febrile neutropenia. (1)
Limitations of Use
RYZNEUTA is not indicated for the mobilization of peripheral blood progenitor cells for hematopoietic stem cell transplantation. (1)

2. DOSAGE AND ADMINISTRATION

- Recommended Dose: 20 mg administered subcutaneously once per chemotherapy cycle. (2.1)
- Administer approximately 24 hours after cytotoxic chemotherapy. Do not administer between 14 days before and 24 hours after administration of cytotoxic chemotherapy. (2.1)

3. DOSAGE FORMS AND STRENGTHS

- Injection: 20 mg/mL solution in a single-dose prefilled syringe. (3)

4. CONTRAINDICATIONS

Patients with a history of serious allergic reactions to granulocyte stimulating factors such as efbemalenograstim alfa-vuxw, pegfilgrastim, or filgrastim products. (4)

5. WARNINGS AND PRECAUTIONS

- Fatal splenic rupture: Evaluate patients who report left upper abdominal or shoulder pain for an enlarged spleen or splenic rupture. (5.1)
- Acute respiratory distress syndrome (ARDS): Evaluate patients who develop fever, lung infiltrates, or respiratory distress. Discontinue RYZNEUTA in patients with ARDS. (5.2)
- Serious allergic reactions, including anaphylaxis: Permanently discontinue RYZNEUTA in patients with serious allergic reactions. (5.3)
- Sickle cell crises in Patients with Sickle Cell Disorders: Discontinue RYZNEUTA if sickle cell crisis occurs. (5.4)
- Glomerulonephritis: Evaluate and consider dose-reduction or interruption of RYZNEUTA if causality is likely. (5.5)
- Thrombocytopenia: Monitor platelet counts. (5.7)
- Capillary Leak Syndrome: Monitor patients with symptoms; consider intensive care. (5.8)
- Myelodysplastic Syndrome (MDS) and Acute Myeloid Leukemia (AML) in Patients with Breast and Lung Cancer: Monitor patients with breast and lung cancer using RYZNEUTA in conjunction with chemotherapy and/or radiotherapy for signs and symptoms of MDS/AML. (5.10)

6. ADVERSE REACTIONS

Most common adverse reactions (≥10%) were nausea, anemia, and thrombocytopenia. (6.1)

To report SUSPECTED ADVERSE REACTIONS, contact Acrotech Biopharma Inc at 1-888-292-9617 or FDA at 1-800-FDA-1088 or www.fda.gov/medwatch.

FULL PRESCRIBING INFORMATION

1. INDICATIONS AND USAGE

RYZNEUTA is indicated to decrease the incidence of infection, as manifested by febrile neutropenia, in adult patients with non-myeloid malignancies receiving myelosuppressive anti-cancer drugs associated with a clinically significant incidence of febrile neutropenia.

Limitations of Use

RYZNEUTA is not indicated for the mobilization of peripheral blood progenitor cells for hematopoietic stem cell transplantation.

2. DOSAGE AND ADMINISTRATION

2.1 Recommended Dosage

The recommended dosage of RYZNEUTA is a single subcutaneous injection of 20 mg administered once per chemotherapy cycle at least 24 hours after cytotoxic chemotherapy. Do not administer RYZNEUTA within 14 days before and <24 hours after administration of cytotoxic chemotherapy.

2.2 Administration

RYZNEUTA is administered subcutaneously via a single-dose prefilled syringe by a healthcare professional.

Prior to use‚ remove the carton from the refrigerator (keeping the prefilled syringe inside the carton) for a minimum of 30 minutes to allow the product to reach room temperature. Discard any product left at room temperature for greater than 48 hours.

Parenteral drug products should be inspected visually for particulate matter and discoloration prior to administration, whenever solution and container permit. Do not administer RYZNEUTA if discoloration or particulates are observed.

Caution: This product contains natural rubber latex which may cause allergic reactions. The needle cap on the prefilled syringe contains natural rubber; people with latex allergies should not administer this product.

The RYZNEUTA prefilled syringe does not bear graduation marks and is intended only to deliver the entire contents of the syringe (20 mg/mL) for direct administration to adult patients.

Administer injection by pinching the skin and holding. Inject into the abdomen, the back or side of the upper arms, or the thighs. Rotate injection sites. Do not inject into scar tissue or areas that are reddened, inflamed, or swollen. If injecting into the abdomen, avoid a 2-inch diameter circle around the navel. Once the entire dose has been injected, the needle safety device will be triggered, pulling the needle automatically from the skin, and into the barrel; the entire needle will be covered by the needle guard.

3. DOSAGE FORMS AND STRENGTHS

Injection: 20 mg/mL clear, colorless, preservative-free solution in a single-dose prefilled syringe.

4. CONTRAINDICATIONS

RYZNEUTA is contraindicated in patients with a history of serious allergic reactions to granulocyte stimulating factors such as efbemalenograstim alfa-vuxw, pegfilgrastim, or filgrastim products [see Warnings and Precautions (5.3)] .

5. WARNINGS AND PRECAUTIONS

5.1 Splenic Rupture

Splenic rupture, including fatal cases, can occur following the administration of recombinant human granulocyte colony-stimulating factor (rhG-CSF) products, such as RYZNEUTA. Evaluate for an enlarged spleen or splenic rupture in patients who report left upper abdominal or shoulder pain after receiving RYZNEUTA.

5.2 Acute Respiratory Distress Syndrome

Acute respiratory distress syndrome (ARDS) can occur in patients receiving rhG-CSF products, such as RYZNEUTA. Evaluate patients who develop fever and lung infiltrates or respiratory distress after receiving RYZNEUTA for ARDS. Discontinue RYZNEUTA in patients with ARDS.

5.3 Serious Allergic Reactions

Serious allergic reactions, including anaphylaxis, can occur in patients receiving rhG-CSF products, such as RYZNEUTA. Permanently discontinue RYZNEUTA in patients with serious allergic reactions. RYZNEUTA is contraindicated in patients with a history of serious allergic reactions to RYZNEUTA or other rhG-CSF products such as pegfilgrastim, eflapegrastim or filgrastim products.

5.4 Sickle Cell Crisis in Patients with Sickle Cell Disorders

Severe and sometimes fatal sickle cell crises can occur in patients with sickle cell disorders receiving rhG-CSF products, such as RYZNEUTA. Discontinue RYZNEUTA if sickle cell crisis occurs.

5.5 Glomerulonephritis

Glomerulonephritis has occurred in patients receiving rhG-CSF products. The diagnoses were based upon azotemia, hematuria (microscopic and macroscopic), proteinuria, and renal biopsy. Generally, events of glomerulonephritis resolved after dose-reduction or discontinuation of rhG-CSF. If glomerulonephritis is suspected, evaluate for cause. If causality is likely, consider dose-reduction or interruption of RYZNEUTA.

5.6 Leukocytosis

White blood cell (WBC) counts of 100 × 10^9/L or greater have been observed in patients receiving rhG-CSF products. Monitor complete blood count (CBC) during RYZNEUTA therapy. Discontinue RYZNEUTA treatment if WBC count of 100 × 10^9/L or greater occurs.

5.7 Thrombocytopenia

Thrombocytopenia has been reported in patients receiving rhG-CSF products. Thrombocytopenia occurred in 11% of RYZNEUTA-treated patients. One patient (0.4%) experienced severe thrombocytopenia. Monitor platelet counts.

5.8 Capillary Leak Syndrome

Capillary leak syndrome has been reported after administration of rhG-CSF products and is characterized by hypotension, hypoalbuminemia, edema and hemoconcentration. Episodes vary in frequency and severity, and may be life-threatening if treatment is delayed. Patients who develop symptoms of capillary leak syndrome should be closely monitored and receive standard symptomatic treatment, which may include a need for intensive care.

5.9 Potential for Tumor Growth Stimulatory Effects on Malignant Cells

The granulocyte colony-stimulating factor (G-CSF) receptor through which RYZNEUTA acts has been found on tumor cell lines. The possibility that RYZNEUTA acts as a growth factor for any tumor type, including myeloid malignancies and myelodysplasia, diseases for which RYZNEUTA is not approved, cannot be excluded.

5.10 Myelodysplastic Syndrome (MDS) and Acute Myeloid Leukemia (AML) in Patients with Breast and Lung Cancer

MDS and AML have been associated with the use of rhG-CSF products in conjunction with chemotherapy and/or radiotherapy in patients with breast and lung cancer. Monitor patients for signs and symptoms of MDS/AML in these settings.

5.11 Aortitis

Aortitis has been reported in patients receiving rhG-CSF products. It may occur as early as the first week after start of therapy. Manifestations may include generalized signs and symptoms such as fever, abdominal pain, malaise, back pain, and increased inflammatory markers (e.g., c-reactive protein and white blood cell count). Consider aortitis in patients who develop these signs and symptoms without known etiology. Discontinue RYZNEUTA if aortitis is suspected.

5.12 Nuclear Imaging

Increased hematopoietic activity of the bone marrow in response to growth factor therapy has been associated with transient positive bone imaging changes. This should be considered when interpreting bone imaging results.

6. ADVERSE REACTIONS

The following clinically significant adverse reactions are discussed in greater detail in other sections of the labeling:

- Splenic Rupture [see Warnings and Precautions (5.1)]
- Acute Respiratory Distress Syndrome [see Warnings and Precautions (5.2)]
- Serious Allergic Reactions [see Warnings and Precautions (5.3)]
- Sickle Cell Crisis in Patients with Sickle Cell Disorders [see Warnings and Precautions (5.4)]
- Glomerulonephritis [see Warnings and Precautions (5.5)]
- Leukocytosis [see Warnings and Precautions (5.6)]
- Thrombocytopenia [see Warnings and Precautions (5.7)]
- Capillary Leak Syndrome [see Warnings and Precautions (5.8)]
- Potential for Tumor Growth Stimulatory Effects on Malignant Cells [see Warnings and Precautions (5.9)]
- Myelodysplastic Syndrome (MDS) and Acute Myeloid Leukemia (AML) in Patients with Breast and Lung Cancer [see Warnings and Precautions (5.10)]
- Aortitis [see Warnings and Precautions (5.11)]

6.1 Clinical Trials Experience

Because clinical trials are conducted under widely varying conditions, adverse reaction rates observed in the clinical trials of a drug cannot be directly compared with rates in the clinical trials of another drug and may not reflect the rates observed in clinical practice.

The following adverse reaction data are based on two studies [see Clinical Studies (14)]. The first was a randomized, double-blind, placebo-controlled study in patients with metastatic or non-metastatic breast cancer receiving doxorubicin 60 mg/m^2 and docetaxel 75 mg/m^2 every 21 days (Study GC-627-04). A total of 122 female patients were randomized to receive either 20 mg RYZNEUTA (n=83) or placebo (n=39) in chemotherapy cycle 1; all patients received RYZNEUTA in cycles 2-4. The second was a randomized, open-label, active-controlled study in patients with stage I to III invasive breast cancer receiving docetaxel 75 mg/m^2 and cyclophosphamide 600 mg/m^2 (Study GC-627-05). A total of 393 patients were randomized to receive either 20 mg RYZNEUTA (n=197) or pegfilgrastim (n=196) in chemotherapy cycles 1 through 4.

In Study GC-627-04, the most common adverse reactions (≥10%) in the RYZNEUTA arm through cycle 1 were nausea, anemia, and thrombocytopenia (see Table 1). Other adverse reactions reported by ≥ 20% of RYZNEUTA-treated Patients with Breast Cancer Receiving Myelosuppressive Chemotherapy in Study GC-627-05 were fatigue and bone pain.

Table 1. Adverse Reactions [Adverse reactions that occurred in ≥10% of Ryzneuta-treated patients and ≥5% more than placebo-treated patients.] in Study GC-627-04 in RYZNEUTA-treated Patients with Breast Cancer Receiving Myelosuppressive Chemotherapy Through Cycle 1
Adverse Reactions | Ryzneuta (n=83) | Placebo (n=39)
Nausea | 42 (51) | 15 (39)
Anemia | 12 (15) | 4 (10)
Thrombocytopenia | 10 (12) | 1 (3)

8. USE IN SPECIFIC POPULATIONS

8.1 Pregnancy

Risk Summary
Although available data with RYZNEUTA use in pregnant women are insufficient to establish whether there is a drug associated risk of major birth defects, miscarriage, or adverse maternal or fetal outcomes, there are available data from published studies in pregnant women exposed to other human G-CSF products. These studies have not established an association of G-CSF product use during pregnancy with major birth defects, miscarriage, or adverse maternal or fetal outcomes.

In animal studies, no evidence of reproductive/developmental toxicity occurred in the offspring of pregnant rats and rabbits that received cumulative doses of efbemalenograstim alfa-vuxw approximately 2.6 and 0.7 times, respectively, the recommended human dose (based on body surface area).

The estimated background risk of major birth defects and miscarriage for the indicated population is unknown. All pregnancies have a background risk of birth defect, loss, or other adverse outcomes. In the U.S. general population, the estimated background risks of major birth defects and miscarriage in clinically recognized pregnancies is 2-4% and 15-20%, respectively.

Data
Animal Data

Three studies were conducted in pregnant rats dosed with efbemalenograstim alfa-vuxw at cumulative doses up to approximately 2.6 times the recommended human dose at the following stages of gestation: during the period of organogenesis, from mating through the first half of pregnancy, and from the first trimester through delivery and lactation. No evidence of fetal loss or structural malformations was observed in any study. Growth and learning were also unaffected.

Pregnant rabbits were dosed with efbemalenograstim alfa-vuxw every other day during organogenesis at cumulative doses up to 0.7 times the recommended human dose showed no signs of fetal loss or structural malformations.

Maternal toxicity (decreased weight gain or weight loss and/or death) was observed when higher cumulative doses of efbemalenograstim alfa-vuxw were used in an early dose-ranging study in rabbits.

8.2 Lactation

Risk Summary

There are no data on the presence of efbemalenograstim alfa-vuxw or its metabolite in either human or animal milk, the effects on the breastfed child, or the effects on milk production. The developmental and health benefits of breastfeeding should be considered along with the mother’s clinical need for efbemalenograstim alfa-vuxw and any potential adverse effects on the breastfed child from efbemalenograstim alfa-vuxw or from the underlying maternal condition.

8.4 Pediatric Use

Safety and effectiveness in pediatric patients have not been established.

8.5 Geriatric Use

Clinical studies of RYZNEUTA did not include sufficient numbers of subjects aged 65 and over to determine whether they respond differently from younger subjects. Other reported clinical experience with RYZNEUTA has not identified differences in responses between the elderly and younger patients.

10. OVERDOSAGE

Overdosage of RYZNEUTA may result in leukocytosis and bone pain. In the event of overdose, general supportive measures should be instituted, as necessary. Monitor the patient for adverse reactions [see Adverse Reactions (6)] .

11. DESCRIPTION

Efbemalenograstim alfa-vuxw, a leukocyte growth factor, is a 413 amino acid recombinant fusion protein consisting of human G-CSF, a 16 amino-acid linker, and the Fc portion of human IgG2. In solution, efbemalenograstim alfa-vuxw forms covalently-linked dimers (disulfide bonds between Fc moieties), resulting in an immunoglobulin-like structure. The dimer is a water-soluble, glycosylated protein with a molecular weight of approximately 93.4 kilodaltons (kDa), of which 89.5 kDa is attributed to amino acids (protein sequence) and the remainder is from glycosylation. Efbemalenograstim alfa-vuxw is obtained from genetically-engineered strain of Chinese hamster ovary (CHO) cells grown in a serum-free medium.

RYZNEUTA (efbemalenograstim alfa-vuxw) injection is supplied in 1 mL prefilled single-dose syringes for manual subcutaneous injection. The prefilled syringe does not bear graduation marks and is designed to deliver the entire contents of the syringe (20 mg/mL). Each syringe contains 20 mg efbemalenograstim alfa-vuxw in a sterile, clear, colorless, preservative-free solution (pH 5.2) containing acetate (0.6 mg), EDTA (0.29 mg), polysorbate 20 (0.1 mg), sodium (0.23 mg), and sorbitol (50 mg) in Water for Injection, USP.

12. CLINICAL PHARMACOLOGY

12.1 Mechanism of Action

Efbemalenograstim alfa-vuxw is a colony-stimulating factor that acts on hematopoietic cells by binding to specific cell surface receptors, thereby stimulating proliferation, differentiation, commitment, and end cell functional activation.

12.2 Pharmacodynamics

Over the tested dose range of 30 to 360 μg/kg in healthy adult males, neutrophils generally increased in a dose-dependent manner; however, the effect on neutrophils plateaued at the top two doses of 240 and 360 μg/kg.

In patients with breast cancer given EC chemotherapy, in cycle 1, median ANC peaked on Day 4 (about 24 hours after efbemalenograstim alfa-vuxw administration) for the 240 and 320 μg/kg doses, declined to nadir on Days 8–9, and then recovered to a count of 2.0 × 10^9/L and higher by Day 11. The ANC levels in cycles 2, 3, and 4 tended to be higher than those observed in cycle 1.

In patients with breast cancer given TAC chemotherapy, in cycle 1, median ANC peaked on Day 3 (about 24 hours after efbemalenograstim alfa-vuxw administration) in cycle 1 and 3, reached nadir on Day 8, and recovered to 2.0 x 10^9/L on Days 9 and 10 for the 320 μg/kg and 240 μg/kg doses, respectively. Mean ANC nadir was higher with 320 μg/kg compared to 240 μg/kg in both cycle 1 (0.75 x 10^9/L and 0.29 x 10^9/L, respectively), and cycle 3 (1.19 x 10^9/L and 0.57 x 10^9/L, respectively).

12.3 Pharmacokinetics

The pharmacokinetics of efbemalenograstim alfa-vuxw was studied in female patients with breast cancer and healthy male subjects. Efbemalenograstim alfa-vuxw exhibited nonlinear and time-dependent pharmacokinetics over the dose range of 30 to 360 μg/kg. At the approved recommended dose in healthy subjects, the mean (%CV) Cmaxwas 1202 ng/mL (56%), and the AUC0-infwas 76357 h*ng/mL (65%). At the approved recommended dose in patients with breast cancer, the geometric mean (CV%) Cmax was 1085 ng/mL (92%) in Cycle 1 and 525 ng/mL (163%) in Cycle 3; the geometric mean (CV%) AUC0-infwas 54858 h*ng/mL (110%) in Cycle 1 and 26217 h*ng/mL (167%) in Cycle 3.

Absorption

The median tmax of efbemalenograstim alfa-vuxw administered as 80 to 320 μg/kg in female patients with breast cancer receiving EC chemotherapy ranged from 24 hours to 48 hours in Cycle 1 and 9 to 30 hours in Cycle 3. The median tmax of efbemalenograstim alfa-vuxw administered as 240 to 320 μg/kg in female participants with breast cancer receiving TAC chemotherapy was 36 hours in Cycle 1 and ranged from 24 to 30 hours in Cycle 3.

Distribution

The geometric mean (CV%) apparent volume of distribution of efbemalenograstim alfa-vuxw was 18.8 L (257%) in Cycle 1 and 40.7 L (387%) in Cycle 3 in female patients with breast cancer.

Elimination

The geometric mean (CV%) apparent clearance of efbemalenograstim alfa-vuxw was 0.36 L/h (110%) in Cycle 1 and 0.76 L/h (167%) in Cycle 3. The geometric mean (CV%) elimination half-life of efbemalenograstim alfa-vuxw was 35.6 h (108%) in Cycle 1 and 36.9 h (120%) in Cycle 3. Neutrophil receptor binding is an important component of the clearance of efbemalenograstim alfa-vuxw, and serum clearance is directly related to the number of neutrophils.

Metabolism

Efbemalenograstim alfa-vuxw is expected to be metabolized into small peptides by catabolic pathways.

Specific Populations

No clinically significant differences were observed based on age (20 to 83 years) or body weight (40 to 137 kg) [see Use in Specific Populations (8.5)]. The impact of sex, race/ethnicity, renal impairment, hepatic impairment, and pregnancy on the pharmacokinetics of efbemalenograstim alfa-vuxw are unknown.

12.6 Immunogenicity

The observed incidence of anti-drug antibodies is highly dependent on the sensitivity and specificity of the assay. Differences in assay methods preclude meaningful comparisons of the incidence of anti-drug antibodies in the studies described below with the incidence of anti-drug antibodies in other studies, including those of efbemalenograstim alfa-vuxw or of other efbemalenograstim alfa products.

During the 3-month treatment period and 6-month follow-up in studies GC-627-04, GC-627-05 and SP11631, 20/438 (4.6%) RYZNEUTA-treated subjects developed treatment-emergent anti-drug antibodies to efbemalenograstim alfa-vuxw (3/121, 17/197 and 0/120, respectively). Additionally, 16/438 (3.7%) of RYZNUETA-treated subjects developed treatment-emergent antibodies to G-CSF (1/121, 15/197 and 0/120, respectively). None of these patients who were positive for antibodies to efbemalenograstim alfa-vuxw or G-CSF had evidence of neutralizing antibodies using a cell-based bioassay, and there was no evidence of altered pharmacokinetics or allergic-type reactions. In Study GC-627-05, the incidence of antibodies to G-CSF was similar in patients treated with RYZNEUTA (15/197, 7.6%) and pegfilgrastim (13/195, 6.7%). None of these patients had evidence of neutralizing antibodies to G-CSF based on a cell-based bioassay and clinical observations, including absolute neutrophil counts.

13. NONCLINICAL TOXICOLOGY

13.1 Carcinogenesis, Mutagenesis, Impairment of Fertility

No carcinogenicity or mutagenesis studies have been conducted with efbemalenograstim alfa-vuxw.

Efbemalenograstim alfa did not affect reproductive performance or fertility in male or female rats at cumulative weekly doses approximately 2.2 times higher than the recommended human dose (based on body surface area).

14. CLINICAL STUDIES

The efficacy of RYZNEUTA to decrease the incidence of infection, as manifested by febrile neutropenia, in patients with nonmyeloid malignancies receiving myelosuppressive anti-cancer drugs was evaluated in two randomized, controlled studies.

Study GC-627-04 [NCT02872103] was a randomized, double-blind, placebo-controlled study that employed doxorubicin 60 mg/m^2 and docetaxel 75 mg/m^2 administered every 21 days for up to 4 cycles for the treatment of metastatic or non-metastatic breast cancer. In this study, 122 patients were randomized to receive a single subcutaneous injection of RYZNEUTA (20 mg) or placebo on day 2 of chemotherapy cycle 1. All patients received RYZNEUTA (20 mg) on day 2 of chemotherapy cycles 2 – 4. The patients were 30 to 69 years of age and all female. The race was 99% Caucasian, and 1% Black. The ethnicity was 2% Hispanic or Latino.

Efficacy was based upon the mean duration of severe (Grade 4) neutropenia in cycle 1 which was lower for RYZNEUTA-treated patients as compared to placebo-treated patients (LS mean: 1.4 days versus 4.3 days, respectively, p<0.001 [95% CI: 2.4, 3.5]). The incidence of febrile neutropenia (defined as temperature ≥38.3℃, or >38.0℃ sustained for at least 1 hour, and ANC < 0.5 × 10^9/L) was also lower for RYZNEUTA-treated patients compared to placebo-treated patients in cycle 1 (4.8% versus 25.6%, respectively, p=0.0016; 20.8% difference [95% CI: 1.8%, 38.8%].

Study GC-627-05 [NCT03252431] was a randomized, active-controlled study that compared RYZNEUTA to pegfilgrastim. Study GC-627-05 employed docetaxel 75 mg/m^2and cyclophosphamide 600 mg/m^2administered every 21 days for up to 4 cycles for the treatment of non-metastatic breast cancer. In this study, 393 patients were randomized to receive a single subcutaneous injection of RYZNEUTA (20 mg) or pegfilgrastim (6 mg) on day 2 of each chemotherapy cycle. The patients were 26 to 83 years of age and all female and Caucasian. The ethnicity was 0.3% Hispanic or Latino.

The study demonstrated that the mean days of severe (Grade 4) neutropenia of RYZNEUTA-treated patients did not exceed that of pegfilgrastim-treated patients by more than 0.6 days in cycle 1 of chemotherapy. The mean days of severe neutropenia in cycle 1 were 0.2 days in both the RYZNEUTA and pegfilgrastim arms (difference in means 0.0 days [95% CI -0.1, 0.1]).

Subgroup analyses of treatment effect were not useful due to small subgroup sizes.

16. HOW SUPPLIED/STORAGE AND HANDLING

RYZNEUTA (efbemalenograstim alfa-vuxw) injection is a clear, colorless, preservative-free solution supplied in a prefilled single-dose syringe with a 27-gauge, 1/2-inch needle and an UltraSafe Passive™ Needle Guard, containing 20 mg of efbemalenograstim alfa-vuxw.

Caution: This product contains natural rubber latex which may cause allergic reactions. The needle cap of the prefilled syringe contains natural rubber; persons with latex allergies should not administer this product.

RYZNEUTA is provided in a dispensing pack containing one 20 mg/mL prefilled syringe (NDC 72893-016-02).

RYZNEUTA prefilled syringe does not bear graduation marks and is intended only to deliver the entire contents of the syringe (20 mg/mL) for direct administration to adult patients.

Store refrigerated at 2°C to 8°C (36°F to 46°F) in the carton to protect from light. Do not shake. Discard syringes stored at room temperature for more than 48 hours. Do not freeze. Discard syringe if frozen.

17. PATIENT COUNSELING INFORMATION

Advise the patient to read the FDA-approved patient labeling (Patient Information)

Advise patients of the following risks and potential risks with RYZNEUTA:

- Rupture or enlargement of the spleen may occur. Symptoms include left upper quadrant abdominal pain or left shoulder pain. Advise patients to report pain in these areas to their healthcare provider immediately [see Warnings and Precautions (5.1)] .
- Dyspnea, with or without fever, progressing to acute respiratory distress syndrome, may occur. Advise patients to report dyspnea to their healthcare provider immediately [see Warnings and Precautions (5.2)] .
- Serious allergic reactions may occur, which may be signaled by rash, facial edema, wheezing, dyspnea, hypotension, or tachycardia. Advise patients to seek immediate medical attention if signs or symptoms of hypersensitivity reaction occur [see Warnings and Precautions (5.3)] .
- In patients with sickle cell disease, sickle cell crisis and death have occurred with use of human granulocyte colony-stimulating factors. Discuss potential risks and benefits for patients with sickle cell disease prior to the administration of RYZNEUTA [see Warnings and Precautions (5.4)] .
- Glomerulonephritis may occur. Symptoms include swelling of the face or ankles, dark colored urine or blood in the urine, or a decrease in urine production. Advise patients to report signs or symptoms of glomerulonephritis to their healthcare provider immediately [see Warnings and Precautions (5.5)] .
- Capillary leak syndrome may occur. Symptoms include hypotension and edema. Advise patients to report signs and symptoms of capillary leak syndrome to their healthcare provider immediately [see Warnings and Precautions (5.9)] .
- There may be an increased risk of Myelodysplastic Syndrome and/or Acute Myeloid Leukemia in patients with breast and lung cancer who receive RYZNEUTA in conjunction with chemotherapy and/or radiation therapy. Symptoms of MDS and AML may include tiredness, fever, and easy bruising or bleeding. Advise patients to report to their physician signs and symptoms of MDS/AML [see Warnings and Precautions (5.9)] .
- Aortitis may occur. Symptoms may include fever, abdominal pain, malaise, back pain, and increased inflammatory markers. Advise patients to report signs and symptoms of aortitis to their physician immediately [see Warnings and Precautions (5.11)] .

RYZNEUTA®(efbemalenograstim alfa-vuxw)

Manufactured by:

EVIVE BIOTECHNOLOGY SINGAPORE PTE. LTD.
Singapore, 189720

Distributed by: Acrotech Biopharma Inc, East Windsor, NJ 08520 USA

U.S. License No 2248

© 2023 Evive Biotechnology Singapore PTE. LTD.

For more information, go to www.ryzneuta.com or call 1-888-292-9617

Patient Information
RYZNEUTA® (rīz-new-ta)
(efbemalenograstim alfa-vuxw)
injection
Single-Dose Prefilled Syringe

What is RYZNEUTA?
RYZNEUTA is a is a man-made form of granulocyte colony-stimulating factor (G-CSF). G-CSF is a substance produced by the body. It stimulates the growth of neutrophils, a type of white blood cell important in the body’s fight against infection.

- RYZNEUTA is used in adults.
- It is not known if RYZNEUTA is safe and effective in children.

Do not take RYZNEUTAif you have had a serious allergic reaction to granulocyte stimulating factors such as efbemalenograstim alfa-vuxw, pegfilgrastim products or filgrastim products.

Before you receive RYZNEUTA, tell your healthcare provider about all of your medical conditions, including if you:

- have a sickle cell disorder.
- have kidney problems.
- are allergic to latex. The needle cap on the prefilled syringe contains dry natural rubber (derived from latex).
- are pregnant or plan to become pregnant. It is not known if RYZNEUTA will harm your unborn baby.
- are breastfeeding or plan to breastfeed. It is not known if RYZNEUTA passes into your breast milk.

Tell your healthcare provider about all of the medicines you take,including prescription and over-the-counter medicines, vitamins, and herbal supplements.

How will I receive RYZNEUTA?

- RYZNEUTA is given as an injection under your skin (subcutaneous injection) by a healthcare provider.
- RYZNEUTA should be injected at least 24 hours after your dose of chemotherapy and at least 14 days before your next dose of chemotherapy.
- If you miss a dose of RYZNEUTA, talk to your healthcare provider about when you should receive your next dose.

What are possible side effects of RYZNEUTA?
RYZNEUTA may cause serious side effects, including:

- Spleen rupture.Your spleen may become enlarged and can rupture. A ruptured spleen can cause death. Call your healthcare provider right away if you have pain in the left upper stomach area or your left shoulder.
- A serious lung problem called Acute Respiratory Distress Syndrome (ARDS).Call your healthcare provider or get emergency care right away if you have shortness of breath with or without a fever, trouble breathing, or a fast rate of breathing.
- Serious allergic reactions.RYZNEUTA can cause serious allergic reactions. These reactions can cause a rash over your whole body, swelling around your mouth or eyes, wheezing, shortness of breath, dizziness, and fast heart rate. If you have any of these symptoms, stop using RYZNEUTA and call your healthcare provider or get emergency medical help right away.
- Risk of Sickle cell crises.You may have a serious sickle cell crisis, which could lead to death, if you have a sickle cell disorder and receive RYZNEUTA. Call your healthcare provider right away if you have symptoms of sickle cell crisis such as pain or difficulty breathing.
- Kidney injury (glomerulonephritis).Products like RYZNEUTA can cause kidney injury. Call your healthcare provider right away if you develop any of the following symptoms:
  - swelling of your face or ankles
  - dark colored urine or blood in your urine
  - you urinate less than usual
- Increased white blood cell count (leukocytosis).Your healthcare provider will check your blood during treatment with RYZNEUTA.
- Decreased platelet count (thrombocytopenia).Your healthcare provider will check your blood during treatment with RYZNEUTA.
- Capillary Leak Syndrome.RYZNEUTA can cause fluid to leak from blood vessels into your body’s tissues. This condition is called “Capillary Leak Syndrome” (CLS). CLS can quickly cause you to have symptoms that may become life-threatening. Get emergency medical help right away if you develop any of the following symptoms:
  - swelling or puffiness and urinating less than usual
  - trouble breathing
  - swelling of your stomach area (abdomen) and feeling of fullness
  - dizziness or feeling faint
  - a general feeling of tiredness
- Myelodysplastic Syndrome (MDS) and Acute Myeloid Leukemia (AML).If you have breast cancer or lung cancer, when RYZNEUTA is used with chemotherapy and radiation therapy, or with radiation therapy alone, you may have an increased risk of developing a precancerous blood condition called myelodysplastic syndrome (MDS) or a blood cancer called acute myeloid leukemia (AML). Symptoms of MDS and AML may include tiredness, fever, and easy bruising or bleeding. Call your healthcare provider if you develop these symptoms during treatment with RYZNEUTA.
- Inflammation of the aorta (aortitis).Inflammation of the aorta (the large blood vessel that transports blood from the heart to the body) has been reported in patients who received products like RYZNEUTA. Symptoms may include fever, abdominal pain, feeling tired, and back pain. Call your healthcare provider if you experience these symptoms.
- The most common side effects of RYZNEUTAare nausea, anemia, and thrombocytopenia.
- These are not all the possible side effects of RYZNEUTA.
- Call your doctor for medical advice about side effects. You may report side effects to FDA at 1-800-FDA-1088.

General information about the safe and effective use of RYZNEUTA.
Medicines are sometimes prescribed for purposes other than those listed in a Patient Information leaflet. You can ask your pharmacist or healthcare provider for information about RYZNEUTA that is written for health professionals.

What are the ingredients in RYZNEUTA?
Active ingredient:efbemalenograstim alfa-vuxw
Inactive ingredients:acetate, EDTA, polysorbate 20, sodium, and sorbitol in water for injection.
Manufactured by: EVIVE BIOTECHNOLOGY SINGAPORE PTE. LTD., Singapore, 189720

Distributed by: Acrotech Biopharma Inc, East Windsor, NJ 08520 USA
U.S. License No. 2248
© 2023 Evive Biotechnology Singapore PTE. LTD. All rights reserved.
For more information, go to www.ryzneuta.com or call 1-888-292-9617.

This Patient Information has been approved by the U.S. Food and Drug Administration. Revised: 12/2024

Syringe Label

RYZNEUTA

(efbemalenograstim alfa-vuxw)

Injection

20 mg/mL

For Subcutaneous Use Only

Single-dose Prefilled Syringe

Mfr By: EVIVE BIOTECHNOLOGY SINGAPORE PTE. LTD

Dist.By: Acrotech Biopharma Inc, East Windsor, NJ 08520 USA

Carton Label

RYZNEUTA

(efbemalenograstim alfa-vuxw)

Injection

20 mg/mL

Store refrigerated at 2° to 8°C (36° to 46°F) in the
carton to protect from light. Do Not Freeze or Shake.
Sterile Solution - No preservatives

RYZNEUTA NDC 72893-016-02
(efbemalenograstim alfa-vuxw) Rx Only
Injection
20 mg/mL
Recombinant dimeric human granulocyte colony-stimulating factor Fc fusion protein derived from mammalian cell culture
For Subcutaneous Injection by a Healthcare Provider Only
Contains One Single-Dose Prefilled Syringe
Dosage: See Prescribing Information
Manufactured By:
EVIVE BIOTECHNOLOGY SINGAPORE PTE. LTD.
Singapore, 189720

Distributed by: Acrotech Biopharma Inc, East Windsor, NJ 08520 USA
US License No. 2248
Product of China

RYZNEUTA NDC 72893-016-02

(efbemalenograstim alfa-vuxw)
Injection
Rx Only
20 mg/mL
For Subcutaneous Injection by a Healthcare Provider Only
Each 1 mL prefilled syringe contains: 20 mg efbemalenograstim alfa-vuxw in a sterile, clear, colorless
solution (pH 5.2) containing acetate (0.6 mg), EDTA (0.29 mg), polysorbate 20 (0.1 mg), sodium (0.23 mg), and sorbitol (50 mg) in water for injection, USP.
Caution: The Packaging of This Product Contains Natural Rubber Latex Which May Cause Allergic Reactions.

Tray Lid Label

RYZNEUTA

(efbemalenograstim alfa-vuxw)

Injection
20 mg/mL
For Subcutaneous Use Only
Recombinant dimeric human granulocyte colony-stimulating factor Fc fusion protein derived from mammalian cell culture
One Single-Dose Prefilled Syringe
Rx Only NDC 72893-016-02

Each 1 mL prefilled syringe contains: 20 mg efbemalenograstim alfa-vuxw in a sterile, clear, colorless solution (pH 5.2) containing
acetate (0.6 mg), EDTA (0.29 mg), polysorbate 20 (0.1 mg), sodium (0.23 mg), and sorbitol (50 mg) in water for injection, USP

Dosage: See Prescribing Information
Store refrigerated at 2° to 8°C (36° to 46°F) in the carton
to protect from light. Do Not Freeze or Shake.

Sterile Solution – No Preservatives

Caution: The Packaging of This Product Contains Natural
Rubber Latex Which May Cause Allergic Reactions.

Mfr. By: EVIVE BIOTECHNOLOGY SINGAPORE PTE. LTD.

Dist. By: Acrotech Biopharma Inc, East Windsor, NJ 08520 USA

US LIC No. 2248